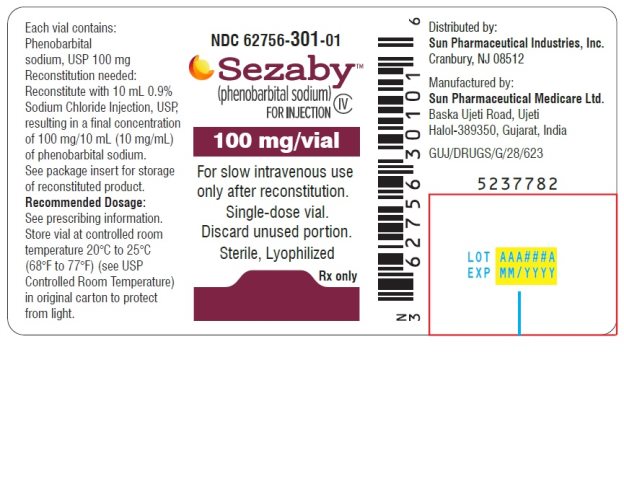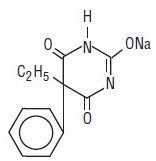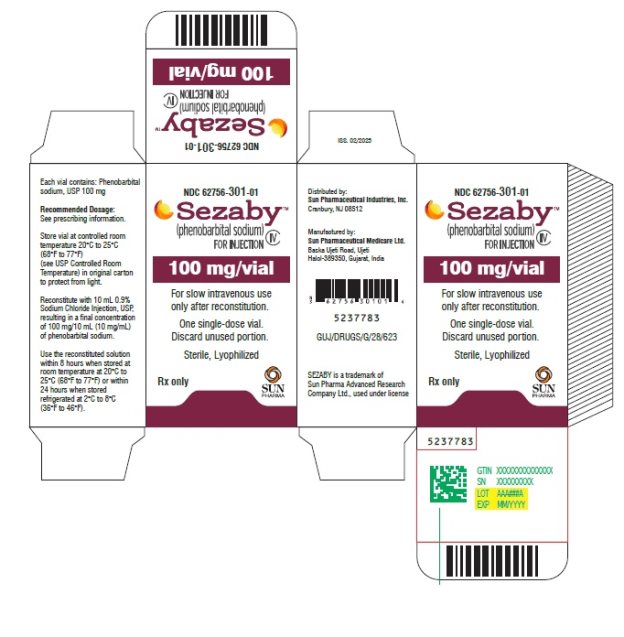 DRUG LABEL: SEZABY
NDC: 62756-301 | Form: INJECTION
Manufacturer: Sun Pharmaceutical Industries, Inc.
Category: prescription | Type: HUMAN PRESCRIPTION DRUG LABEL
Date: 20251223
DEA Schedule: CIV

ACTIVE INGREDIENTS: PHENOBARBITAL SODIUM 100 mg/1 1

HIGHLIGHTS OF PRESCRIBING INFORMATION

These highlights do not include all the information needed to use SEZABY safely and effectively. See full prescribing information for SEZABY.
SEZABY™ (phenobarbital sodium) for injection, for intravenous use, CIV
Initial U.S. Approval: 2022

WARNING: RISKS FROM CONCOMITANT USE WITH OPIOIDS; DEPENDENCE AND WITHDRAWAL REACTIONS AFTER USE OF SEZABY FOR A LONGER DURATION THAN RECOMMENDED; and ABUSE, MISUSE AND ADDICTION WITH UNAPPROVED USE IN ADOLESCENTS AND ADULTS

See full prescribing information for complete boxed warning.

- Concomitant use of phenobarbital products, including SEZABY, and opioids may result in profound sedation, respiratory depression, coma, and death. If a decision is made to use concomitantly, limit dosages and durations to the minimum required, and monitor patients for respiratory depression and sedation. (5.1, 7.3)
- Although SEZABY is indicated only for short-term use (1, 2), if used for a longer duration than recommended, abrupt discontinuation or rapid dosage reduction may precipitate acute withdrawal reactions, which can be life-threatening. For patients receiving SEZABY for a longer duration than recommended, to reduce the risk of withdrawal reactions, use a gradual taper to discontinue SEZABY. (5.2)
- SEZABY is not approved for use in adolescents or adults. The unapproved use of SEZABY in adolescents and adults exposes them to risks of abuse, misuse, and addiction, which can lead to overdose or death. (5.3)

1 INDICATIONS AND USAGE

SEZABY is a barbiturate indicated for the treatment of neonatal seizures in term and preterm infants.

2 DOSAGE AND ADMINISTRATION

- Loading Dose: 20 mg/kg is administered by intravenous infusion over 15 minutes into a large peripheral vein. If clinically indicated, at least 15 minutes after completion of the initial loading dose, a second loading dose may be administered over the subsequent 15 minutes as 20 mg/kg for term infants or 10 mg/kg or 20 mg/kg for preterm infants. The maximum total loading dose is 40 mg/kg. (2.1)
- Maintenance Dosage: starting 8 to 12 hours after first loading dose:
  4.5 mg/kg/day given in 2 or 3 divided doses (i.e., 1.5 mg/kg every 8 hours or 2.25 mg/kg every 12 hours) up to 5 days. (2.1).
- Must be reconstituted with 10 mL 0.9 % Sodium Chloride Injection, USP prior to administration. See additional preparation and administration instructions in the Full Prescribing Information. (2.3)

3 DOSAGE FORMS AND STRENGTHS

For injection: 100 mg of phenobarbital sodium lyophilized powder in a single-dose vial for reconstitution

4 CONTRAINDICATIONS

- Acute porphyrias (4)
- Hypersensitivity to phenobarbital or other barbiturates (4)

5 WARNINGS AND PRECAUTIONS

- Respiratory Depression or Insufficiency: Abnormal respiration has been observed; careful respiratory monitoring is recommended during and after treatment. (5.4)
- Serious Dermatologic Reactions: Serious and sometimes fatal hypersensitivity reactions, including toxic epidermal necrolysis and Stevens-Johnson syndrome, have been reported. SEZABY should be discontinued at the first sign of a rash, unless the rash is clearly not drug related. (5.5)
- Drug Reaction with Eosinophilia and Systemic Symptoms (DRESS)/Multiorgan hypersensitivity: DRESS can be fatal or life-threatening. If signs or symptoms of DRESS are present, evaluate the patient immediately. Discontinue if an alternative etiology cannot be established. (5.6)
- Infusion Site Reactions: SEZABY may cause tissue damage with necrosis; avoid perivascular extravasation or intra-arterial injection. Stop SEZABY if evidence of pain, swelling, discoloration, or temperature change in limb. (5.9)
- QT Prolongation: Avoid concomitant use of SEZABY in patients who are at significant risk of developing torsade de pointes and with products that may increase the risk of the QTc interval prolongation or products that may increase concentrations of SEZABY. (5.10)

6 ADVERSE REACTIONS

The most common adverse reactions (incidence > 5% patients overall) are abnormal respiration, sedation, feeding disorder, and hypotension. (6.1)

To report SUSPECTED ADVERSE REACTIONS, contact Sun Pharmaceutical Industries, Inc. at 1-800-818-4555 or FDA at 1-800-FDA-1088 or www.fda.gov/medwatch.

7 DRUG INTERACTIONS

- CYP2C9, 2C19, 2E1, UGT Inhibitors: Closely monitor and decrease SEZABY dosage, if needed. (7.1)
- CYP3A4, 2B6, 2C, UGT Substrates: Substrate dosage adjustment may be needed. (7.1)
- CNS depressants: Closely monitor for sedation and respiratory depression. (7.2)
- Drugs that Prolong the QT Interval: Avoid concomitant use. (7.3)

FULL PRESCRIBING INFORMATION

WARNING: RISKS FROM CONCOMITANT USE WITH OPIOIDS; DEPENDENCE AND WITHDRAWAL REACTIONS AFTER USE OF SEZABY FOR A LONGER DURATION THAN RECOMMENDED; and ABUSE, MISUSE AND ADDICTION WITH UNAPPROVED USE IN ADOLESCENTS AND ADULTS

Risks from Concomitant Use with Opioids

Concomitant use of phenobarbital products, including SEZABY, and opioids may result in profound sedation, respiratory depression, coma, and death. Reserve concomitant prescribing of these drugs for patients for whom alternative treatment options are inadequate. If a decision is made for concomitant use of these drugs, limit dosages and durations to the minimum required, and follow patients for signs and symptoms of respiratory depression and sedation [see Warnings and Precautions (5.1) and Drug Interactions (7.3)].

Dependence and Withdrawal Reactions After Use of SEZABY for a Longer Duration than Recommended

The continued use of phenobarbital may lead to clinically significant physical dependence. The risks of dependence and withdrawal increase with longer treatment duration and higher daily dose. Although SEZABY is indicated only for short-term use [see Indications and Usage (1) and Dosage and Administration (2)], if used for a longer duration than recommended, abrupt discontinuation or rapid dosage reduction of SEZABY may precipitate acute withdrawal reactions, which can be life-threatening. For patients receiving SEZABY for longer duration than recommended, to reduce the risk of withdrawal reactions, use a gradual taper to discontinue SEZABY [see Warnings and Precautions (5.2)].

Abuse, Misuse, and Addiction with Unapproved Use in Adolescents and Adults

SEZABY is not approved for use in adolescents or adults. The unapproved use of SEZABY, in adolescents and adults exposes them to risks of abuse, misuse, and addiction, which can lead to overdose or death. Abuse and misuse of phenobarbital commonly involve concomitant use of other drugs, alcohol, and/or illicit substances, which is associated with an increased frequency of serious adverse outcomes [see Warnings and Precaution (5.3)].

1 INDICATIONS AND USAGE

SEZABY is indicated for the treatment of neonatal seizures in term and preterm infants.

2 DOSAGE AND ADMINISTRATION

2.1 Recommended Dosage and Administration

The recommended dosage of SEZABY in neonates consists of a loading dose(s) followed by maintenance dosage (see Table 1). Administer SEZABY by intravenous infusion (over 15 minutes) into a large peripheral vein to avoid local tissue toxicity [see Warnings and Precautions (5.9)]. SEZABY is for intravenous use only.

Table 1: Recommended Dosage of SEZABY for Neonatal Seizures

Loading Dose (maximum total loading dose is 40 mg/kg)
First loading dose | 20 mg/kg
Second loading dose; (If clinically indicated)^1 | Preterm Infants | 10 mg/kg or 20 mg/kg [see Clinical Pharmacology (12.3)]
Second loading dose; (If clinically indicated)^1 | Term Infants | 20 mg/kg
Maintenance Dosage (total daily dose is 4.5 mg/kg/day and the total duration is up to 5 days)
Initiate 8 to 12 hours after first loading dose
Option 1 | 1.5 mg/kg every 8 hours
Option 2 | 2.25 mg/kg every 12 hours

^1If seizures persist or recur any time 15 minutes after completion of the initial loading dose, administer a second loading dose. (Administer the second loading dose no sooner than 15 minutes after completion of the first loading dose.)

2.2 Reconstitution and Additional Administration Instructions

- Determine the number of vials to be reconstituted based on the patient’s weight and recommended dose.
- Aseptically reconstitute the lyophilized powder in the vial using 10 mL of 0.9% Sodium Chloride Injection, USP.
- Swirl the vial gently until contents are completely dissolved.
  - The reconstituted solution contains 100 mg per 10 mL (10 mg/mL) of phenobarbital sodium.
  - Inspect the vial visually for particulate matter and discoloration prior to administration (the reconstituted solution is clear, colorless, and free from visible particulate matter).
- Discard the reconstituted solution if it is discolored or contains foreign particles.
- Withdraw the appropriate volume from the reconstituted vial for intravenous infusion and administer immediately [see Dosage and Administration (2.3)].
- Discard any unused portion of the reconstituted solution left in the vial [see Description (11)].

2.3 Storage of Reconstituted Solution

If the reconstituted solution is not administered immediately, place the vial back in the original carton to protect it from light and store at either room temperature at 20°C to 25°C (68°F to 77°F) for a maximum of 8 hours or in the refrigerator at 2°C to 8°C (36°F to 46°F) for a maximum of 24 hours. Discard any unused portion of the reconstituted solution after the recommended storage duration.

3 DOSAGE FORMS AND STRENGTHS

For injection: 100 mg of phenobarbital sodium as a white to off-white lyophilized powder in a single-dose vial for reconstitution.

4 CONTRAINDICATIONS

SEZABY is contraindicated in patients with:

- acute porphyrias [see Warnings and Precautions (5.8)], or
- a history of hypersensitivity reaction to phenobarbital or other barbiturates [see Warnings and Precautions (5.7)]

5 WARNINGS AND PRECAUTIONS

5.1 Risks from Concomitant Use with Opioids

Concomitant use of phenobarbital products, including SEZABY, and opioids may result in profound sedation, respiratory depression, coma, and death [see Drug Interactions (7.3)].

Reserve concomitant prescribing of these drugs for patients for whom alternative treatment options are inadequate. If a decision is made for concomitant use of these drugs, limit dosages and durations to the minimum required, and follow patients for signs and symptoms of respiratory depression and sedation. Practitioners administering SEZABY must have the skills necessary to manage serious cardiorespiratory adverse reactions, including skills in airway management.

5.2 Dependence and Withdrawal Reactions After Use of SEZABY for a Longer Duration Than Recommended

The continued use of phenobarbital may lead to clinically significant physical dependence. Although SEZABY is indicated only for short-term use [see Indications and Usage (1) and Dosage and Administration (2)], if used for a longer duration than recommended, abrupt discontinuation or rapid dosage reduction of SEZABY may precipitate acute withdrawal reactions, which can be life-threatening (e.g., seizures) [see Drug Abuse and Dependence (9.3)].

To reduce the risk of withdrawal reactions in patients receiving SEZABY for a longer duration than recommended, use a gradual taper to discontinue SEZABY (a patient-specific plan should be used to taper the dose). Patients at an increased risk of withdrawal adverse reactions after phenobarbital discontinuation or rapid dosage reduction include those who received higher dosages, or those who had longer durations of use.

5.3 Abuse, Misuse, and Addiction with Unapproved Use in Adolescents and Adults

SEZABY is not approved for use in adolescents or adults. The unapproved use of SEZABY in adolescents and adults exposes them to the risks of abuse, misuse, and addiction, which can lead to overdose or death. Abuse and misuse of barbiturates, including phenobarbital, often (but not always) involve the use of doses exceeding the doses used in clinical practice and commonly involve concomitant use of other drugs, alcohol, and/or illicit substances, which is associated with an increased frequency of serious adverse outcomes, including respiratory depression, overdose, or death [see Drug Abuse and Dependence (9.2)].

5.4 Respiratory Depression or Insufficiency

In Study 1, 25% of patients treated with phenobarbital developed abnormal respiration [see Adverse Reactions (6.1) and Clinical Studies (14)]. Careful respiratory monitoring is needed during and after the administration of SEZABY.

5.5 Serious Dermatologic Reactions

Serious and sometimes fatal dermatologic reactions, including toxic epidermal necrolysis (TEN) and Stevens-Johnson syndrome (SJS), have been reported with the use of phenobarbital.

SEZABY should be discontinued at the first sign of a rash, unless the rash is clearly not drug related. If signs or symptoms suggest SJS/TEN, use of SEZABY should not be resumed and alternative therapy should be considered. If a rash occurs, the patient should be evaluated for signs and symptoms of Drug Reaction with Eosinophilia and Systemic Symptoms [see Warnings and Precautions (5.6)].

5.6 Drug Reaction with Eosinophilia and Systemic Symptoms (DRESS)/Multiorgan Hypersensitivity

Drug Reaction with Eosinophilia and Systemic Symptoms (DRESS), also known as multiorgan hypersensitivity, has been reported in patients taking antiepileptic drugs, including phenobarbital. Some of these events have been fatal or life-threatening. DRESS typically, although not exclusively, presents with fever, rash, lymphadenopathy, and/or facial swelling, in association with other organ system involvement, such as hepatitis, nephritis, hematological abnormalities, myocarditis, or myositis sometimes resembling an acute viral infection. Eosinophilia is often present. Because this disorder is variable in its expression, other organ systems not noted here may be involved. It is important to note that early manifestations of hypersensitivity, such as fever or lymphadenopathy, may be present even though rash is not evident.

If such signs or symptoms are present, the patient should be evaluated immediately. SEZABY should be discontinued if an alternative etiology for the signs or symptoms cannot be established.

5.7 Hypersensitivity Reactions

Phenobarbital-associated hypersensitivity reactions may include symptoms and signs such as rash, fever, facial or limb edema, and lymphadenopathy.

SEZABY is contraindicated in patients who have experienced hypersensitivity to phenobarbital or other barbiturates. Additionally, consider alternatives to structurally similar drugs such as carboxamides (e.g., carbamazepine) and hydantoins (e.g., phenytoin) in these same patients. Similarly, if there is a history of hypersensitivity reactions to these structurally similar drugs in the patient or immediate family members, consider alternatives to SEZABY. If signs or symptoms of hypersensitivity reactions are present in a patient treated with SEZABY, the patient should be evaluated immediately and SEZABY should be discontinued if an alternative etiology for the signs or symptoms cannot be established.

5.8 Exacerbation of Porphyria

SEZABY may precipitate acute attacks in patients with acute porphyrias. These episodes may be life-threatening, and include symptoms and signs such as anxiety, confusion, limb or abdominal pain, hyponatremia, seizures, and muscle weakness. Therefore, SEZABY is contraindicated in patients with acute porphyrias [see Contraindications (4)].

5.9 Infusion Site Reactions

SEZABY is highly alkaline [see Description (11)]. Therefore, extreme care should be taken to avoid perivascular extravasation or intra-arterial injection. Extravascular injection may cause local tissue damage with subsequent necrosis; consequences of intraarterial injection may vary from transient pain to gangrene of the limb. Any evidence of pain, swelling, discoloration, or temperature change in the limb warrants stopping the injection.

5.10 QT Prolongation

SEZABY may prolong the QT interval [see Clinical Pharmacology (12.2)].

Avoid use of SEZABY in patients who are at significant risk of developing torsade de pointes, including those with congenital long QT syndrome, uncontrolled or significant cardiac disease, recent myocardial infarction, heart failure, unstable angina, bradyarrhythmias, AV block, aortic stenosis, or uncontrolled hypothyroidism. If use cannot be avoided in these patients, collect ECGs during treatment at specified intervals as clinically indicated, and monitor serum electrolytes and correct abnormalities.

Avoid the concomitant use of products that may increase the risk of QTc interval prolongation or products that may increase concentrations of phenobarbital [see Drug Interactions (7.3)]. If concomitant use of a product that also prolongs the QTc interval or that increases SEZABY concentrations is unavoidable, monitor patients for increased risk of QTc interval prolongation.

5.11 Embryofetal Toxicity with Unapproved Use in Adolescents and Adults

SEZABY is not approved for use in adolescents or adults. Based on findings from prospective controlled trials, cohort studies, pregnancy registries, and randomized controlled-trials, phenobarbital can cause fetal harm when administered during pregnancy. Data from observational studies suggest an increased risk of major congenital malformations in infants of mothers who received phenobarbital during pregnancy.

5.12 Neonatal Adverse Reactions from Unapproved Maternal Phenobarbital Use

SEZABY is not approved for use in adolescents or adults. Phenobarbital crosses the placenta and may produce respiratory depression, hypotonia, and sedation in neonates of mothers who received phenobarbital during pregnancy. The use of SEZABY late in pregnancy can result in the following adverse reactions in neonates:

- Sedation (respiratory depression, lethargy, hypotonia) and/or
- Withdrawal reactions (hyperreflexia, irritability, restlessness, tremors, inconsolable crying and feeding difficulties).

Neonatal coagulation defects have also been reported within the first 24 hours in neonates exposed to phenobarbital during pregnancy.

5.13 Sedation, Respiratory Depression, and Withdrawal in Neonates Exposed to Phenobarbital Through Breast Milk

SEZABY is not approved for use in adolescents or adults. Phenobarbital is present and may accumulate in breast milk. Phenobarbital has been detected in some neonates exposed to breast milk from phenobarbital-treated mothers. There are reports of sedation, respiratory depression and withdrawal in infants exposed to phenobarbital through breast milk.

5.14 Suicidal Behavior and Ideation with Unapproved Use in Adolescents and Adults

SEZABY is not approved for use in adolescents or adults. Antiepileptic drugs (AEDs) increase the risk of suicidal thoughts or behavior in adolescents and adults.

Pooled analyses of 199 placebo-controlled clinical trials (mono- and adjunctive therapy) of 11 different AEDs showed that adult patients randomized to one of the AEDs had approximately twice the risk (adjusted relative risk 1.8, 95% confidence interval [CI]: 1.2, 2.7) of suicidal thinking or behavior compared to adult patients randomized to placebo. In these trials, which had a median treatment duration of 12 weeks, the estimated incidence rate of suicidal behavior or ideation among 27,863 AED-treated adult patients was 0.43%, compared to 0.24% among 16,029 placebo-treated adult patients, representing an increase of approximately one case of suicidal thinking or behavior for every 530 adult patients treated. There were four suicides in drug-treated adult patients in the trials and none in placebo-treated adult patients, but the number was too small to allow any conclusion about AED effect on suicide.

The increased risk of suicidal thoughts or behavior in adults with AEDs was observed as early as one week after starting AED treatment and persisted for the duration of treatment assessed.

6 ADVERSE REACTIONS

The following clinically significant adverse reactions are described elsewhere in the labeling:

- Risks from Concomitant Use with Opioids [see Warnings and Precautions (5.1)]
- Dependence and Withdrawal Reactions After Use of SEZABY for a Longer Duration Than Recommended [see Warnings and Precautions (5.2)]
- Abuse, Misuse, and Addiction with Unapproved Use in Adolescents and Adults [see Warnings and Precautions (5.3)]
- Respiratory Depression or Insufficiency [see Warnings and Precautions (5.4)]
- Serious Dermatologic Reactions [see Warnings and Precautions (5.5)]
- Drug Reaction with Eosinophilia and Systemic Symptoms (DRESS)/Multiorgan Hypersensitivity [see Warnings and Precautions (5.6)]
- Hypersensitivity [see Warnings and Precautions (5.7)]
- Exacerbation of Porphyria [see Warnings and Precautions (5.8)]
- Injection Site Reactions [see Warnings and Precautions (5.9)]
- QT Prolongation [see Warnings and Precautions (5.10)]
- Embryofetal Toxicity with Unapproved Use in Adolescents and Adults [see Warnings and Precautions (5.11)]
- Neonatal Adverse Reactions from Unapproved Maternal Phenobarbital Use [see Warnings and Precautions (5.12)]
- Sedation, Respiratory Depression, and Withdrawal in Neonates Exposed to Phenobarbital Through Breast Milk [see Warnings and Precautions (5.13)]
- Suicidal Behavior and Ideation with Unapproved use in Adolescents and Adults [see Warnings and Precautions (5.14)]

6.1 Clinical Trials Experience

Because clinical trials are conducted under widely varying conditions, adverse reaction rates observed in the clinical trials of a drug cannot be directly compared to rates in the clinical trials of another drug and may not reflect the rates observed in practice.

The Study 1 was a multicenter, randomized, double-blind, active-controlled study in neonates who were experiencing seizures [see Clinical Studies (14)]. Patients were infants younger than 14 days of age with gestational ages between 36 and 44 weeks. Overall, 106 neonates (51 female and 55 male) were randomized to receive either phenobarbital (N=42) or levetiracetam (N=64) as their initial treatment. Patients received up to two 15-minute infusions of their initially assigned treatment (loading dose(s)) followed by maintenance treatment of up to 5 days. Mean durations of phenobarbital and levetiracetam treatments were 4.3 and 4 days, respectively.

Table 2 summarizes the adverse reactions that occurred in 2% or more of neonates in Study 1. Incidences are displayed for neonates who received phenobarbital only and for neonates who received levetiracetam only. Because patients in Study 1 were neonates, adverse reactions that are verbally reported could not be assessed in this study.

Table 2: Adverse Reactions That Occurred in At Least 2% of Neonates Overall in Study 1 by Treatment Received

 | Phenobarbital; (N = 32)*; % | Levetiracetam; (N = 19); %
Respiration abnormal | 25 | 5
Sedation | 16 | 5
Feeding disorder | 16 | 5
Hypotension | 16 | 0
Bradycardia | 3 | 0
Hyponatremia | 3 | 0
Sepsis | 3 | 0

* Fifty-five neonates received both phenobarbital and levetiracetam and they had a similar adverse reaction profile as neonates who received only phenobarbital.

6.2 Postmarketing Experience

The following adverse reactions associated with the use of phenobarbital in neonates were identified in the literature. Because these reactions are reported voluntarily from a population of uncertain size, it is not always possible to reliably estimate their frequency or establish a causal relationship to drug exposure.

- Cardiovascular System: Bradycardia, patent ductus arteriosus
- Dermatologic Reactions: Eczema
- Hepatic: Abnormal liver function
- Musculoskeletal: Hypotonia, absent deep tendon reflexes
- Nervous System: Impaired consciousness, neurological impairment
- Renal: Abnormal kidney function
- Respiratory System: Bronchial secretion, respiratory depression

7 DRUG INTERACTIONS

7.1 Cytochrome P450- or Uridine 5’-diphospho-glucuronosyltransferase (UGT)-Based Interactions

The drug interaction information in Table 3 is based upon published literature in non-neonatal populations, in vitro studies, and the mechanistic knowledge of phenobarbital metabolic pathways [see Clinical Pharmacology (12.3)]. Although the data from the published literature regarding these drug interactions are from non-neonatal populations and the magnitude of the potential drug interactions in neonates have not been characterized, this information still warrants consideration given the potential impact of these possible drug interactions on the safety and efficacy of phenobarbital and CYP2B6, 2C9, 2C19, or UGT substrates in neonates.

Table 3: Drug Interactions with SEZABY

Effects of Other Drugs on SEZABY
CYP2C9, 2C19, 2E1, Uridine 5'-diphospho-glucuronosyltransferases (UGT) Inhibitors or Inducers
Prevention or Management | Closely monitor for adverse reactions (e.g., over sedation, prolonged QTc interval, etc.) when used concomitantly with inhibitors of these enzymes and reduced efficacy (e.g., breakthrough seizure) when used with inducers of these enzymes. Consider titration of the SEZABY maintenance dosage accordingly if concomitant use is unavoidable.
Clinical Effect(s) | Phenobarbital is a substrate of CYP2C9, CYP2C19, CYP2E1, and UGTs [see Clinical Pharmacology (12.3)]. It is likely that concomitant use will result in an increase in phenobarbital exposure when used with these inhibitors and a reduction when used with these inducers, which may increase the risk of SEZABY adverse reactions or reduce efficacy, respectively when concomitant use in neonates.
Effects of Other Drugs on Sezaby
CYP3A, 2B6, 2C(s), UGTs Substrates
Prevention or Management | Closely monitor neonates when SEZABY is used concurrently with substrates of these enzymes and consider increasing the dosage of the substrate accordingly, unless otherwise advised in its Prescribing Information, if concomitant use is unavoidable.
Clinical Effect(s) | Phenobarbital is an inducer of CYP3A, CYP2B6, CYP2C(s), and UGT(s) [see Clinical Pharmacology (12.3)]. It is likely that concomitant use in neonates will result in a decrease in the exposure of these substrates, which may reduce efficacy.

7.2 CNS Depressants

Closely monitor for signs of sedation and respiratory depression with concomitant use of SEZABY with other CNS depressants, including opioids [see Warnings and Precautions (5.1)].

Phenobarbital may cause sedation and respiratory depression [see Warnings and Precautions (5.4) and Adverse Reactions (6.1)]. Other products that may also cause these adverse reactions may have additive pharmacologic effect and may increase the risk of sedation and respiratory depression.

7.3 Drugs that Prolong QT Interval

SEZABY may prolong the QT interval [see Warnings and Precautions (5.10) and Clinical Pharmacology (12.2)]. Other products that may also prolong the QTc interval may have additive effects, and products that may increase concentrations of phenobarbital [see Drug Interactions (7.1)] may increase the QT prolongation risk; therefore, avoid concomitant use of SEZABY and these products. If concomitant use of a product that also prolongs the QTc interval or that increases SEZABY concentrations is unavoidable, monitor patients for increased risk of QTc interval prolongation.

8 USE IN SPECIFIC POPULATIONS

8.4 Pediatric Use

The safety and effectiveness of SEZABY have been established for the treatment of neonatal seizures in term and preterm infants, and the information on this use is discussed throughout the labeling.

Juvenile Animal Studies

In published studies, administration of antiepileptic drugs, including phenobarbital, to neonatal rats during the period of synaptogenesis has been reported to result in widespread apoptotic neurodegeneration in the developing brain and neurobehavioral deficits that persist into adulthood at doses associated with plasma exposures similar to those anticipated at the doses proposed for humans. The synaptogenetic period in rats is generally thought to correspond in humans to the third trimester of pregnancy through the first 3 to 4 years of life.

In rodents, exposure to phenobarbital during the neonatal period has been reported in published literature to result in permanent alterations in male and female reproductive function. Administration of phenobarbital to neonatal rats or hamsters resulted in disruption of testosterone secretory profiles and estrous cyclicity, changes in steroidogenesis, altered sexual behavior, and impaired fertility in adulthood.

9 DRUG ABUSE AND DEPENDENCE

9.1 Controlled Substance

SEZABY contains phenobarbital, a Schedule IV controlled substance.

9.2 Abuse

SEZABY is a barbiturate and a CNS depressant with a potential for misuse, abuse, and addiction with unapproved use in adolescents and adults.

Abuse is the intentional, non-therapeutic use of a drug, even once, for its desirable psychological or physiological effects. Misuse is the intentional use, for therapeutic purposes, of a drug by an individual in a way other than prescribed by a health care provider or for whom it was not prescribed. Drug addiction is a cluster of behavioral, cognitive, and physiological phenomena that may include a strong desire to take the drug, difficulties in controlling drug use (e.g., continuing drug use despite harmful consequences, giving a higher priority to drug use than other activities and obligations), and possible tolerance or physical dependence. Even taking barbiturates as prescribed may put patients at risk for abuse and misuse of their medication. Abuse and misuse of barbiturates, including phenobarbital, may lead to addiction.

Abuse and misuse of barbiturates often (but not always) involve the use of doses exceeding the doses used in clinical practice and commonly involve concomitant use of other medications, alcohol, and/or illicit substances, which is associated with an increased frequency of serious adverse outcomes, including respiratory depression, overdose, or death. Barbiturates, including phenobarbital, are often sought by individuals who abuse drugs and other substances, and by individuals with addictive disorders [see Warnings and Precautions (5.3)].

Symptoms of acute intoxication with barbiturates include unsteady gait, slurred speech, and sustained nystagmus. Mental signs of chronic intoxication include confusion, poor judgment, irritability, insomnia, and somatic complaints. The use of phenobarbital alone can result in death; however, death is more often associated with phenobarbital use in the context of polysubstance use (especially with other CNS depressants, such as opioids and alcohol).

9.3 Dependence

Physical Dependence

SEZABY may produce physical dependence. Physical dependence is a state that develops as a result of physiological adaptation in response to repeated drug use, manifested by withdrawal signs and symptoms after abrupt discontinuation or a significant dose reduction of a drug. Abrupt discontinuation or rapid dosage reduction of SEZABY may precipitate acute withdrawal reactions, including seizures, which can be life-threatening. Patients at an increased risk of withdrawal adverse reactions after SEZABY discontinuation or rapid dosage reduction include those administered higher dosages (i.e., higher and/or more frequent doses) and those who have had longer durations of use [see Warnings and Precautions (5.2)].

Symptoms of barbiturate withdrawal, including with phenobarbital, can be severe and may cause life threatening seizures or death.

- Minor withdrawal symptoms may appear 8 to 12 hours after the last barbiturate dose. These symptoms usually appear in the following order: anxiety, muscle twitching, tremor of hands and fingers, progressive weakness, dizziness, distortion in visual perception, nausea, vomiting, insomnia, and orthostatic hypotension.
- Major withdrawal symptoms (convulsions and delirium) may occur within 16 hours and last up to 5 days after abrupt cessation of barbiturates.

The intensity of withdrawal symptoms gradually declines over a period of approximately 15 days.

To reduce the risk of withdrawal reactions in patients using SEZABY for longer durations than recommended, use a gradual taper to discontinue SEZABY over an extended period of time (weeks to months) [see Warnings and Precautions (5.2)].

Tolerance

Tolerance to barbiturates may develop after continued use. Tolerance is a physiological state characterized by a reduced response to a drug after repeated administration (i.e., a higher dose of a drug is required to produce the same effect that was once obtained at a lower dose). As tolerance to barbiturates develops, the amount needed to maintain the same level of intoxication increases; tolerance to a fatal dosage, however, does not increase more than two-fold. As this occurs, the margin between an intoxicating dosage and a fatal dosage becomes smaller.

10 OVERDOSAGE

Overdosage of barbiturates, including phenobarbital, is characterized by central nervous system depression ranging from drowsiness to coma.

- In mild to moderate cases, symptoms can include drowsiness, confusion, dysarthria, lethargy, hypnotic state, diminished reflexes, ataxia, and hypotonia.
- Rarely, paradoxical or disinhibitory reactions (including agitation, irritability, impulsivity, violent behavior, confusion, restlessness, excitement, and talkativeness) may occur.
- In severe overdosage cases, patients may develop respiratory depression and coma.
- Overdosage of barbiturates, particularly in combination with other CNS depressants (including alcohol and opioids) may be fatal [see Warnings and Precautions (5.3)].
- Markedly elevated blood pressure, heart rate, or respiratory rate raise the concern that additional drugs are involved in the overdosage.

In managing SEZABY overdosage, employ general supportive measures, including intravenous fluids, pressors, and airway maintenance. Consider contacting a poison center (1-800-221-2222) or a medical toxicologist for additional overdosage management recommendations.

11 DESCRIPTION

Phenobarbital is a barbiturate. Chemically, phenobarbital sodium is 2,4,6(1H,3H,5H)-Pyrimidinetrione, 5-ethyl-5-phenyl-, monosodium salt and has the following structural formula:

C12H11N2NaO3 MW 254.22

The sodium salt of phenobarbital occurs as a white, slightly bitter powder, crystalline granules or flaky crystals; it is very soluble in water, soluble in alcohol and practically insoluble in ether or chloroform.

SEZABY (phenobarbital sodium) for injection, for intravenous use, is supplied as sterile white to off white lyophilized powder in a 10 mL tubular glass vial. Each single-dose vial contains 100 mg of phenobarbital sodium, USP (equivalent to 91.35 mg of phenobarbital). The pH range is 9.20-10.00. SEZABY does not contain benzyl alcohol or propylene glycol.

12 CLINICAL PHARMACOLOGY

12.1 Mechanism of Action

The precise mechanism of action for phenobarbital for the treatment of neonatal seizures is not fully understood, but it is thought to involve potentiation of synaptic inhibition through an action on the GABAA receptor.

12.2 Pharmacodynamics

Phenobarbital exposure-response relationships and the time course of pharmacodynamic response of phenobarbital in neonates are unknown.

Cardiac Electrophysiology

The effect of SEZABY on the QTc interval has not been adequately characterized. Nonclinical data suggest a potential for phenobarbital to inhibit the hERG potassium cardiac ionic channel, and QTc prolongation was reported in the literature in adult patients with post-stroke seizures at a mean phenobarbital dose of 130 mg (approximately 1.5 times the recommended loading dose in an average 4.4 kg neonate at 4 weeks) [see Indications and Usage (1), Dosage and Administration (2.1), and Warnings and Precautions (5.10)].

12.3 Pharmacokinetics

Mean (± standard deviation) total (bound + unbound) phenobarbital concentrations were evaluated (see Table 4) in term infants younger than 14 days old with gestational ages between 36 and 44 weeks who received either one loading dose (20 mg/kg) or two loading doses (20 mg/kg each) based upon seizure persistence or reoccurrence [see Clinical Studies 14)]. The loading dose(s) was followed by a maintenance dosage of 1.5 mg/kg every 8 hours (total daily dose 4.5 mg/kg/day).

A clinically significant difference between term and preterm infants in phenobarbital PK following the first SEZABY loading dose was not predicted. A second loading dose of either 10 mg/kg or 20 mg/kg of phenobarbital in preterm infants is expected to result in similar plasma concentrations compared to a second loading dose of 20 mg/kg in term infants. In addition, administration of a phenobarbital maintenance dosage of 1.5 mg/kg every 8 hours or 2.25 mg/kg every 12 hours is not expected to result in a clinically significant difference in total phenobarbital plasma concentrations.

Table 4: Observed Phenobarbital Concentration Following Intravenous Phenobarbital Administration in Study 1

Time (Hours) | Phenobarbital Concentration (mcg/mL)
 | One Loading Dose Followed by the Maintenance Dosage | Two Loading Doses^1 Followed by the Maintenance Dosage
1 | 23 (± 2.7) | 26 (± 5.8)
24 | 23 (± 1.3) | 39 (± 9.1)
48 | 25 (± 1.8) | 39 (± 8.2)

^1 Second loading dose administered if seizures persisted or reoccurred more than 15 minutes after the first infusion

Elimination

Published literature reports that the elimination t1/2 of phenobarbital in neonates is approximately 1 week.

Metabolism

Published literature reports that phenobarbital is primarily metabolized by CYP2C9 and to a lesser extent by CYP2C19, CYP2E1, and UGTs. At birth, expression of CYP2C9 is negligible, which results in the longer half-life in neonates compared to older populations in the published literature.

Specific Populations

There are no clinically significant differences in pharmacokinetics of phenobarbital in neonates administered therapeutic hypothermia. The effect of sex, race, ethnicity, renal impairment, or hepatic impairment on phenobarbital pharmacokinetics in neonates is unknown.

Drug Interaction Studies

Clinical Studies and Published Literature

No dedicated clinical studies have been conducted in neonates that evaluated the effect of concomitant use of SEZABY with:

• CYP2C9, 2C19, 2E1, or UGT inhibitors or inducers on phenobarbital pharmacokinetics

• CYP2B6, 2C9, 2C19, or UGT substrates on the pharmacokinetics of these substrates

Published literature regarding these interactions in non-neonatal populations should not be used to estimate the magnitude of the change in phenobarbital exposure in neonates due to differences in the expression of CYP2C9 and possibly other phenobarbital metabolic enzymes in term and preterm infants.

Midazolam: Published literature reports a 2.3-fold increase in the clearance of midazolam (CYP3A substrate) with concurrent use with phenobarbital in 68 neonates with hypoxic ischemic encephalopathy [see Drug Interactions (7.1)].

Theophylline or Chloramphenicol: Published literature reports no change in theophylline or chloramphenicol clearance with concomitant use of phenobarbital in neonates.

In Vitro Studies

Cytochrome P450 (CYP) Enzymes: Phenobarbital is an inhibitor of CYP2B6, CYP2C8, CYP2C9, CYP2C19, and CYP3A4. Phenobarbital is an inducer of CYP3A4, CYP2B6, and CYP2Cs [see Drug Interactions (7.1)].

Uridine diphosphate (UDP)-glucuronosyl transferase (UGT) Enzymes: Phenobarbital is an inhibitor of UGT1A1 and UGT2B7. Published literature reports that phenobarbital is an inducer for UGTs [see Drug Interactions (7.1)].

Transporter Systems: Phenobarbital is an inhibitor of BCRP, OAT1, OAT3, OCT2, OATP1B1, MATE1, and MATE2K. Phenobarbital is not a substrate of OAT1, OAT3, OCT2, OATP1B1, OATP1B3, MATE1, or MATE2K transporters.

13 NONCLINICAL TOXICOLOGY

13.1 Carcinogenesis, Mutagenesis, Impairment of Fertility

Carcinogenesis

Phenobarbital is a rodent carcinogen that has been demonstrated to produce hepatocellular adenomas and carcinomas in rats and mice following lifetime administration.

Mutagenesis

The genotoxic potential of phenobarbital has not been adequately assessed.

Impairment of Fertility

In a published study, administration of phenobarbital (subcutaneous doses up to 60 mg/kg/day) to adult rats prior to and during mating and continuing throughout pregnancy was reported to produce no adverse effects on fertility.

14 CLINICAL STUDIES

The effectiveness of phenobarbital for the treatment of neonatal seizures was established in a randomized, double-blind, active-controlled study in neonates who were experiencing seizures (Study 1; NCT01720667). Patients were neonates younger than 14 days of age with gestational ages between 36 and 44 weeks. Fifty-two percent of patients were male. Fifty-six percent of patients were White, 9% were Native Hawaiian or other Pacific Islander, 5% were Black or African American, 5% were Asian, 4% were mixed race, 1% were American Indian or Alaska Native, and 22% were identified as other, or were missing or unknown. Twenty-six percent of patients were Hispanic or Latino, 60% were not Hispanic or Latino, and 14% were not reported, missing, or unknown.

Eligible patients who experienced electrographically-confirmed seizures were randomized to receive either intravenous phenobarbital (N=42) or levetiracetam (N=64).

- Patients received an initial 15-minute infusion (loading dose) of either 20 mg/kg phenobarbital or 40 mg/kg levetiracetam.
- If electroencephalographic seizures persisted or recurred any time 15 minutes after the initial infusion completion, an additional infusion of the same treatment was administered (the second loading dose was 20 mg/kg infused over 15 minutes for both drugs).
- After loading dose(s) of phenobarbital or levetiracetam were administered, maintenance dosing of that treatment was administered regardless of whether seizures subsided. Maintenance regimens of 1.5 mg/kg/dose of phenobarbital and/or 10 mg/kg/dose of levetiracetam were administered via infusion every 8 hours and continued for up to 5 days. Mean durations of phenobarbital and levetiracetam treatments were 4.3 and 4 days, respectively.

- If seizures persisted or recurred any time 15 minutes after the second loading dose was completed, the patient also received alternate treatment.

The primary endpoint in Study 1 was the percentage of neonates whose seizures were terminated for at least 24 hours without the need for a second drug for the treatment of their seizures. A total of 94 patients who had neurophysiologist-confirmed seizures were included in the efficacy analysis.

Efficacy Results

A statistically significantly greater percentage of phenobarbital-treated patients met Study 1’s primary efficacy endpoint, compared to levetiracetam-treated patients. Table 5 presents the results of the trial’s primary and secondary efficacy analyses.

Table 5: Seizure Efficacy Results in Neonates (Study 1)

 | Phenobarbital (N=33) | Levetiracetam (N=61) | P-value*
Primary Endpoint
Percentage of patients with seizure termination > 24 hours^1 | 73% | 25% | <0.001
Secondary Endpoints
Percentage of patients with seizure termination > 48 hours^1 | 55% | 13% | <0.001
Percentage of patients with seizure termination > 1 hour^1 | 85% | 43% | <0.001**
^1 Without need for a second drug to treat seizures
N = Total number of patients in each treatment group.
*P-value was based on two-sided Fisher’s Exact Test for categorical variables comparing phenobarbital and levetiracetam groups.
**Nominal: not controlled for Type I error
The outcome of 11 patients who had missing data (3 in the phenobarbital group and 8 in the levetiracetam group) was imputed as not successfully terminating seizures.

16 HOW SUPPLIED/STORAGE AND HANDLING

16.1 How Supplied

SEZABY (phenobarbital sodium) for injection is supplied as a sterile white to off-white, lyophilized powder in single-dose clear glass vials containing 100 mg of phenobarbital sodium.

Carton Contents | NDC
One 100 mg single-dose vial | NDC 62756-301-01

The vial stopper is not made with natural rubber latex.

16.2 Storage and Handling

Store unopened vials of SEZABY in original cartons at 20°C to 25°C (68°F to 77°F); excursions permitted between 15°C and 30°C (59°F and 86°F) [see USP Controlled Room Temperature]. Retain in the original carton until use to protect from light.

For information on storage of the reconstituted SEZABY, see Dosage and Administration (2.3).

Manufactured by:

Sun Pharmaceutical Medicare Ltd.,

Baska Ujeti Road, Ujeti,

Halol -389350, Gujarat, India

Distributed by:

Sun Pharmaceutical Industries, Inc.,

Cranbury, NJ 08512

ISS. 02/2023

5237784

SEZABY is a trademark of Sun Pharma Advanced Research Company Ltd., used under license

PACKAGE/LABEL PRINCIPAL DISPLAY PANEL - Vial Label

NDC 62756-301-01

SezabyTM (phenobarbital sodium) for injection CIV

100 mg/vial

For slow intravenous use only after reconstitution.

Single-dose vial.

Discard unused portion.

Sterile, Lyophilized

Rx only

Package/Label Display Panel – Carton Label

NDC 62756-301-01

SezabyTM (phenobarbital sodium) for injection CIV

100 mg/vial

For slow intravenous use only after reconstitution.

Single-dose vial.

Discard unused portion.

Sterile, Lyophilized

Rx only